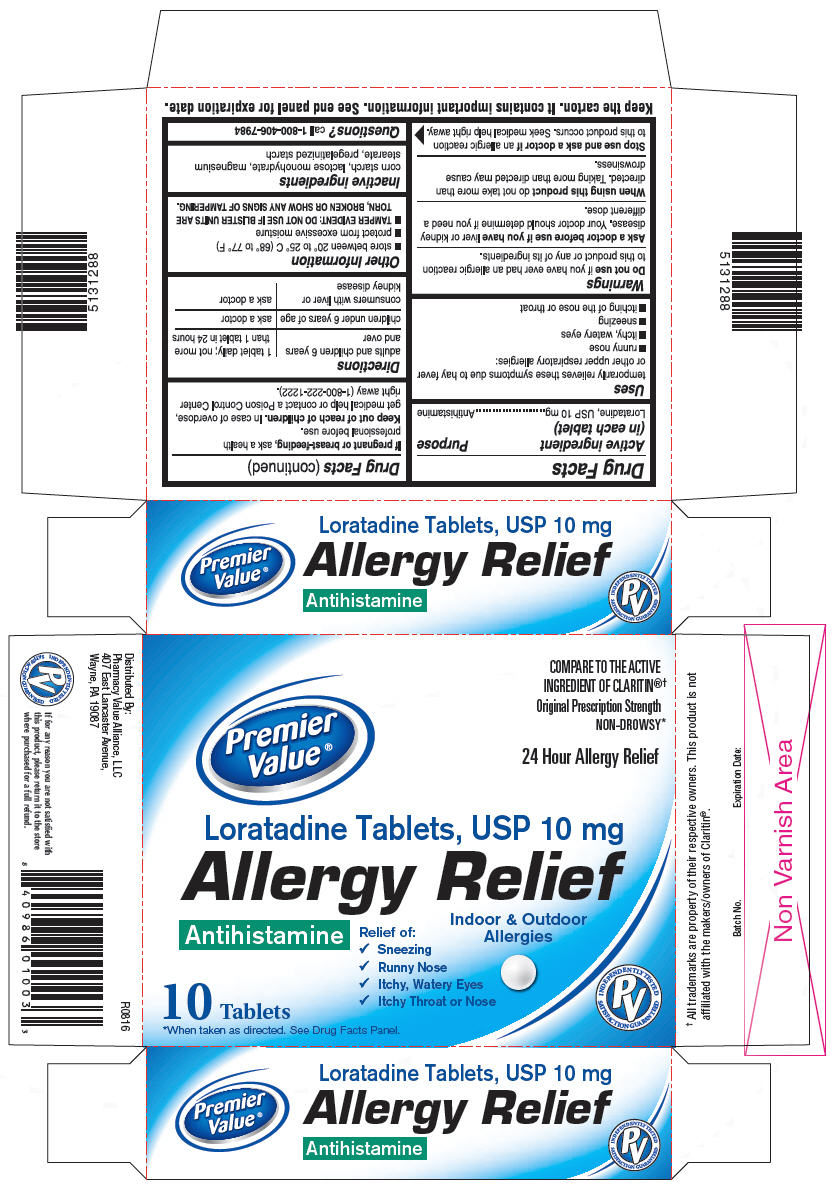 DRUG LABEL: Loratadine
NDC: 68016-526 | Form: TABLET
Manufacturer: Premier Value
Category: otc | Type: HUMAN OTC DRUG LABEL
Date: 20180111

ACTIVE INGREDIENTS: LORATADINE 10 mg/1 1
INACTIVE INGREDIENTS: STARCH, CORN; LACTOSE MONOHYDRATE; MAGNESIUM STEARATE

Drug Facts

ACTIVE INGREDIENT (IN EACH TABLET)

Loratadine USP, 10 mg

PURPOSE

Antihistamine

USES

temporarily relieves these symptoms due to hay fever or other upper respiratory allergies:

- runny nose
- itchy, watery eyes
- sneezing
- itching of the nose or throat

WARNINGS

Do not use

if you have ever had an allergic reaction to this product or any of its ingredients.

Ask a doctor before use if you have

liver or kidney disease. Your doctor should determine if you need a different dose.

When using this product

do not take more than directed. Taking more than directed may cause drowsiness.

Stop use and ask a doctor if

an allergic reaction to this product occurs. Seek medical help right away.

If pregnant or breast-feeding,

ask a health professional before use.

Keep out of reach of children.

In case of overdose, get medical help or contact a Poison Control Center right away.

DIRECTIONS

adults and children 6 years and over | 1 tablet daily; not more than 1 tablet in 24 hours
children under 6 years of age | ask a doctor
consumers with liver or kidney disease | ask a doctor

OTHER INFORMATION

- store between 20 and 25° C (68 and 77° F)
- protect from excessive moisture
- TAMPER EVIDENT: DO NOT USE IF BLISTER UNITS ARE TORN, BROKEN OR SHOW ANY SIGNS OF TAMPERING.
- TAMPER EVIDENT: DO NOT USE IF IMPRINTED SEAL IS BROKEN OR MISSING FROM BOTTLE.

INACTIVE INGREDIENTS

corn starch, lactose monohydrate, magnesium stearate, pregelatinized starch

QUESTIONS?

call 1-800-406-7984

Keep the carton. It contains important information.

See end panel for expiration date.

DISTRIBUTED BY

CHAIN DRUG CONSORTIUM

3301 NW BOCA RATON BLVD

SUITE 101, BOCA RATON, FL 33431

PRINCIPAL DISPLAY PANEL - 10 mg Tablet Blister Pack Carton

Premier
Value®

COMPARE TO THE ACTIVE
INGREDIENT OF CLARITIN®†

Original Prescription Strength
NON-DROWSY*

24 Hour Allergy Relief

Loratadine Tablets, USP 10 mg

Allergy Relief

Indoor & Outdoor
Allergies

Antihistamine

Relief of:

✔ Sneezing
✔ Runny Nose
✔ Itchy, Watery Eyes
✔ Itchy Throat or Nose

10 Tablets

*When taken as directed. See Drug Facts Panel.

INDEPENDENTLY TESTED
PV
SATISFACTION GUARANTEED